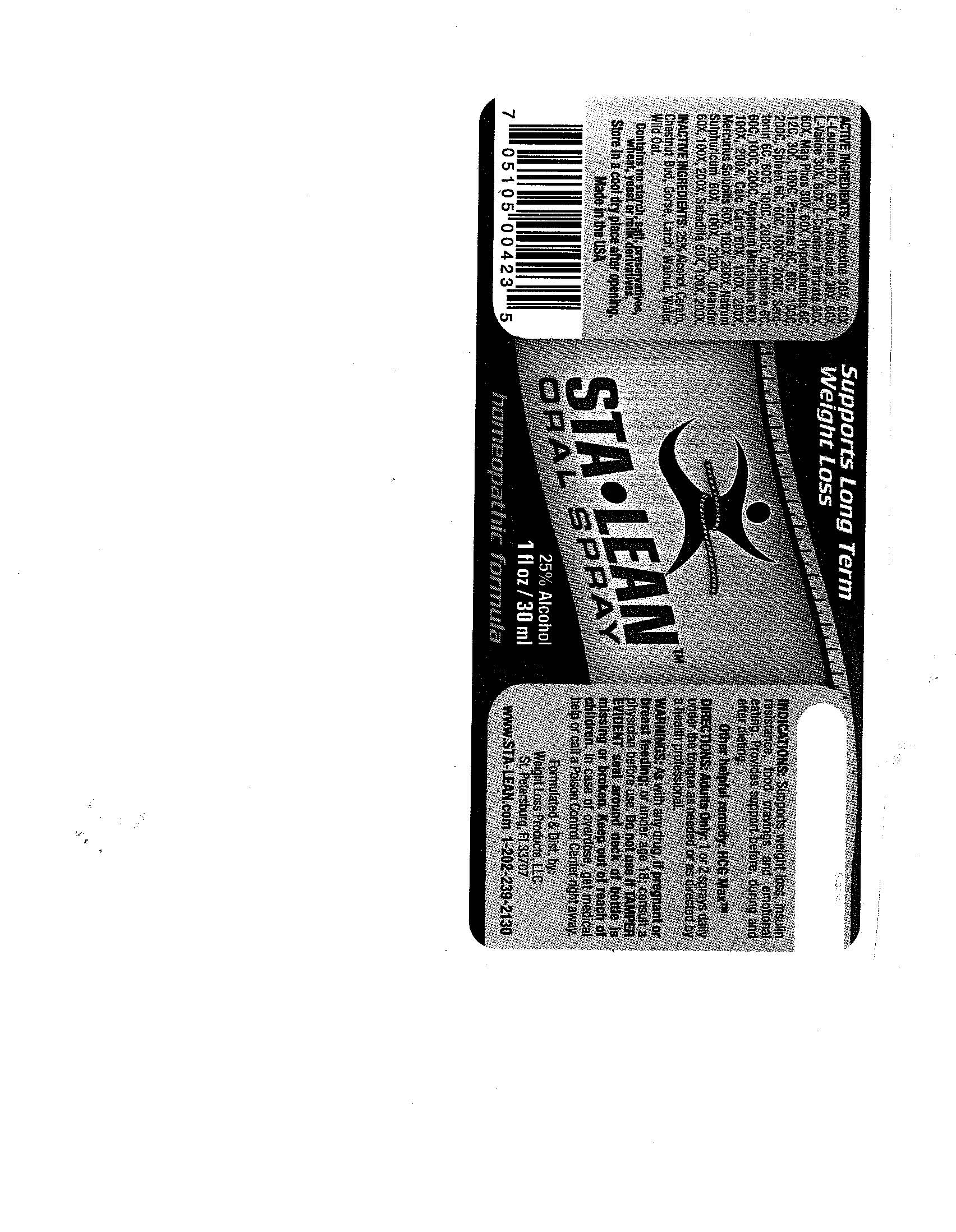 DRUG LABEL: StaLean
NDC: 57520-0190 | Form: SPRAY
Manufacturer: Apotheca Company
Category: homeopathic | Type: HUMAN OTC DRUG LABEL
Date: 20100713

ACTIVE INGREDIENTS: MAGNESIUM PHOSPHATE, DIBASIC TRIHYDRATE 60 [hp_X]/1 mL; PYRIDOXINE 60 [hp_X]/1 mL; SILVER 200 [hp_X]/1 mL; OYSTER SHELL CALCIUM CARBONATE, CRUDE 200 [hp_X]/1 mL; MERCURIUS SOLUBILIS 200 [hp_X]/1 mL; SODIUM SULFATE 200 [hp_X]/1 mL; NERIUM OLEANDER LEAF 200 [hp_X]/1 mL; SCHOENOCAULON OFFICINALE SEED 200 [hp_X]/1 mL; SUS SCROFA HYPOTHALAMUS 100 [hp_C]/1 mL; DOPAMINE 200 [hp_C]/1 mL; SUS SCROFA PANCREAS 200 [hp_C]/1 mL; SEROTONIN 200 [hp_C]/1 mL; SUS SCROFA SPLEEN 200 [hp_C]/1 mL; LEUCINE 60 [hp_X]/1 mL; VALINE 60 [hp_X]/1 mL; ISOLEUCINE 60 [hp_X]/1 mL; LEVOCARNITINE TARTRATE 60 [hp_X]/1 mL
INACTIVE INGREDIENTS: WATER; ALCOHOL; AVENA SATIVA POLLEN; CERATOSTIGMA WILLMOTTIANUM FLOWER; LARIX DECIDUA FLOWERING TOP; JUGLANS REGIA FLOWERING TOP; ULEX EUROPAEUS; AESCULUS CARNEA FLOWER

StaLean

ACTIVE INGREDIENT

Active Ingredients: L Carnitine Tartrate 30X, 60X, L Isoleucine 30X, 60X, L Leucine 30X, 60X, L Valine 30X, 60X, Magnesia Phosphorica 30X, 60X, Pyridoxine 30X, 60X, Argentum Metallicum 60X, 100X, 200X, Calcarea Carbonica 60X, 100X, 200X, Mercurius Solubilis 60X, 100X, 200X, Natrum Sulphuricum 60X, 100X, 200X, Oleander 60X, 100X, 200X, Sabadilla 60X, 100X, 200X, Hypothalamus 6C, 12C, 30C, 100C, Dopamine 6C, 60C, 100C, 200C, Pancreas 6C, 60C, 100C, 200C, Serotonin 6C. 60C, 100C, 200C, Spleen 6C, 60C, 100C, 200C.

PURPOSE

Indications: Supports weight loss, insulin resistance, food cravings and emotional eating. Provides support before, during and after dieting.

Other helpful remedy; HCG Max

WARNINGS

WARNINGS: As with any drug,if pregnant or breast-feeding; or under age 18; consult a physician before use. Do not use if TAMPER EVIDENT seal around neck of bottle is missing or broken. Keep out of reach of children. In case of overdose, get medical help or call a Poison Control Center right away.

Store in a cool, dry place after opening.

DOSAGE AND ADMINISTRATION

DIRECTIONS: Adults Only; 1 or 2 sprays daily under the tongue as needed or as directed by a health professional.

INACTIVE INGREDIENT

Inactive Ingredients: Demineralized Water, 25% Ethanol, Cerato, Chestnut Bud, Gorse, Larch, Walnut, Wild Oat.

QUESTIONS

Formulated and Dist. by:

Weight Loss Products, LLC

St. Petersburg, FL 33707

www.STA-LEAN.com

1-202-239-2130

PACKAGE LABEL

SUPPORTS LONG TERM WEIGHT LOSS

STA.LEAN

ORAL SPRAY

1 FL OZ / 30 ML

HOMEOPATHIC FORMULA